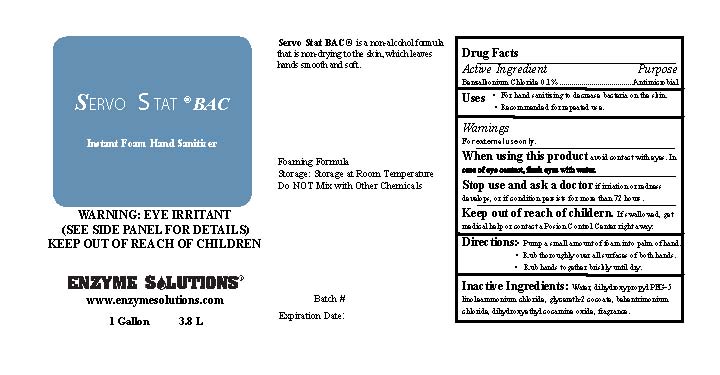 DRUG LABEL: Servo Stat BAC
                
NDC: 76378-020 | Form: LIQUID
Manufacturer: Enzyme Solutions, Inc.
Category: otc | Type: HUMAN OTC DRUG LABEL
Date: 20131114

ACTIVE INGREDIENTS: BENZALKONIUM CHLORIDE 1 mg/1 mL
INACTIVE INGREDIENTS: WATER; DIHYDROXYPROPYL PEG-5 LINOLEAMMONIUM CHLORIDE; GLYCERETH-2 COCOATE; BEHENTRIMONIUM CHLORIDE; DIHYDROXYETHYL COCAMINE OXIDE

Drug Facts

Active Ingredient

Benzalkonium Chloride 0.1%

Purpose

Antimicrobial

Uses

For hand sanitizing to decrease bacteria on the skin.

Recommended for repeated use.

Warnings

For external use only.

When using this product avoid contact with eyes.

In case of eye contact, flush eyes with water.

Stop use and ask a doctor if irritation or redness develops, or if condition persists for more than 72 hours.

Keep out of reach of children.

If swallowed, get medical help or contact a Poison Control Center right away.

Directions

Pump a small amount of foam into palm of hand.

Rub thoroughly over all surfaces of both hands.

Rub hands to gether briskly until dry.

Inactive Ingredients

Water, dihydroxypropyl PEG-5 linoleammonium chloride, glycereth-2 cocoate, behentrimonium chloride, dihydroxyethyl cocamine oxide, fragrance.

PACKAGE LABEL

Servo Stat BAC

Instant Foam Hand Sanitizer

WARNING: EYE IRRITANT

(SEE SIDE PANEL FOR DETAILS)

KEEP OUT OF REACH OF CHILDREN

ENZYME SOLUTIONS

wwww.enzymesolutions.com

1 Gallon 3.8 L

Servo Stat BAC is a non-alcohol formula

that is non-drying to the skin, which leaves

hands smooth and soft.

Foaming Formula

Storage: Store at Room Temperature.

Do NOT Mix with Other Chemicals.

Batch

Expiration Date